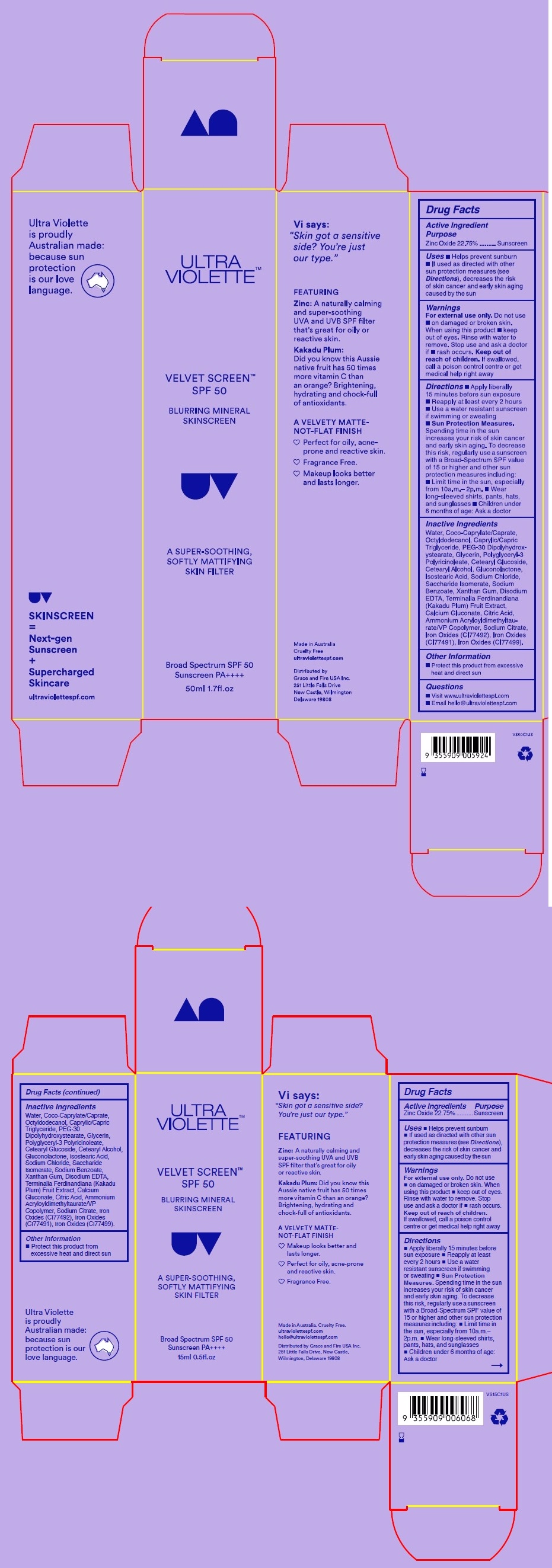 DRUG LABEL: ULTRA VIOLETTE VELVET SCREEN BLURRING MINERAL SKINSCREEN
NDC: 30807-1060 | Form: CREAM
Manufacturer: Wild Child Laboratories PTY Ltd
Category: otc | Type: HUMAN OTC DRUG LABEL
Date: 20260106

ACTIVE INGREDIENTS: ZINC OXIDE 22.75 g/100 mL
INACTIVE INGREDIENTS: OCTYLDODECANOL; EDETATE DISODIUM; CI 77499; PEG-30 DIPOLYHYDROXYSTEARATE; SODIUM CITRATE; XANTHAN GUM; COCO-CAPRYLATE/CAPRATE; CETEARYL GLUCOSIDE; SODIUM BENZOATE; SODIUM CHLORIDE; SACCHARIDE ISOMERATE; KAKADU PLUM; CI 77492; WATER; ISOSTEARIC ACID; CALCIUM GLUCONATE; GLYCERIN; CI 77491; CAPRYLIC/CAPRIC TRIGLYCERIDE; CITRIC ACID ACETATE; 2-ACETAMIDO-2-DEOXY-D-GLUCONO-1,5-LACTONE; AMMONIUM ACRYLOYLDIMETHYLTAURATE/VP COPOLYMER; POLYGLYCERYL-3 PENTARICINOLEATE; CETEARYL ALCOHOL

ULTRA VIOLETTE VELVET SCREEN BLURRING MINERAL SKINSCREEN

Active Ingredients

ZINC OXIDE 22.75%

Purpose

Sunscreen

Uses

Uses  Helps prevent sunburn
 If used as directed with other sun
protection measures (see Directions),
decreases the risk of skin cancer and
early skin aging caused by the sun

Warnings

For External use Only

Do not use

- on damaged or broken skin, when using this product

- keep out of eyes rinse with water to remove

Stop use and ask doctor if

- rash occur

Keep out of reach of children

if swallowed , call a poison control centre or get medical help right away

Directions

 Apply liberally 15 minutes before
sun exposure  Reapply at least
every 2 hours  Use a water
resistant sunscreen if swimming
or sweating  Sun Protection
Measures. Spending time in the sun
increases your risk of skin cancer
and early skin aging. To decrease
this risk, regularly use a sunscreen
with a Broad-Spectrum SPF value of
15 or higher and other sun protection
measures including:  Limit time in
the sun, especially from 10a.m.–
2p.m.  Wear long-sleeved shirts,
pants, hats, and sunglasses
 Children under 6 months of age:
Ask a doctor

Inactive Ingredients

Water, Coco-Caprylate/Caprate,
Octyldodecanol, Caprylic/Capric
Triglyceride, PEG-30
Dipolyhydroxystearate, Glycerin,
Polyglyceryl-3 Polyricinoleate,
Cetearyl Glucoside, Cetearyl Alcohol,
Gluconolactone, Isostearic Acid,
Sodium Chloride, Saccharide
Isomerate, Sodium Benzoate,
Xanthan Gum, Disodium EDTA,
Terminalia Ferdinandiana (Kakadu
Plum) Fruit Extract, Calcium
Gluconate, Citric Acid, Ammonium
Acryloyldimethyltaurate/VP
Copolymer, Sodium Citrate, Iron
Oxides (CI77492), Iron Oxides
(CI77491), Iron Oxides (CI77499).

Other Information

Protect this product from excessive heat and direct sun

Broad Spectrum SPF 50
Sunscreen PA++++
15ml